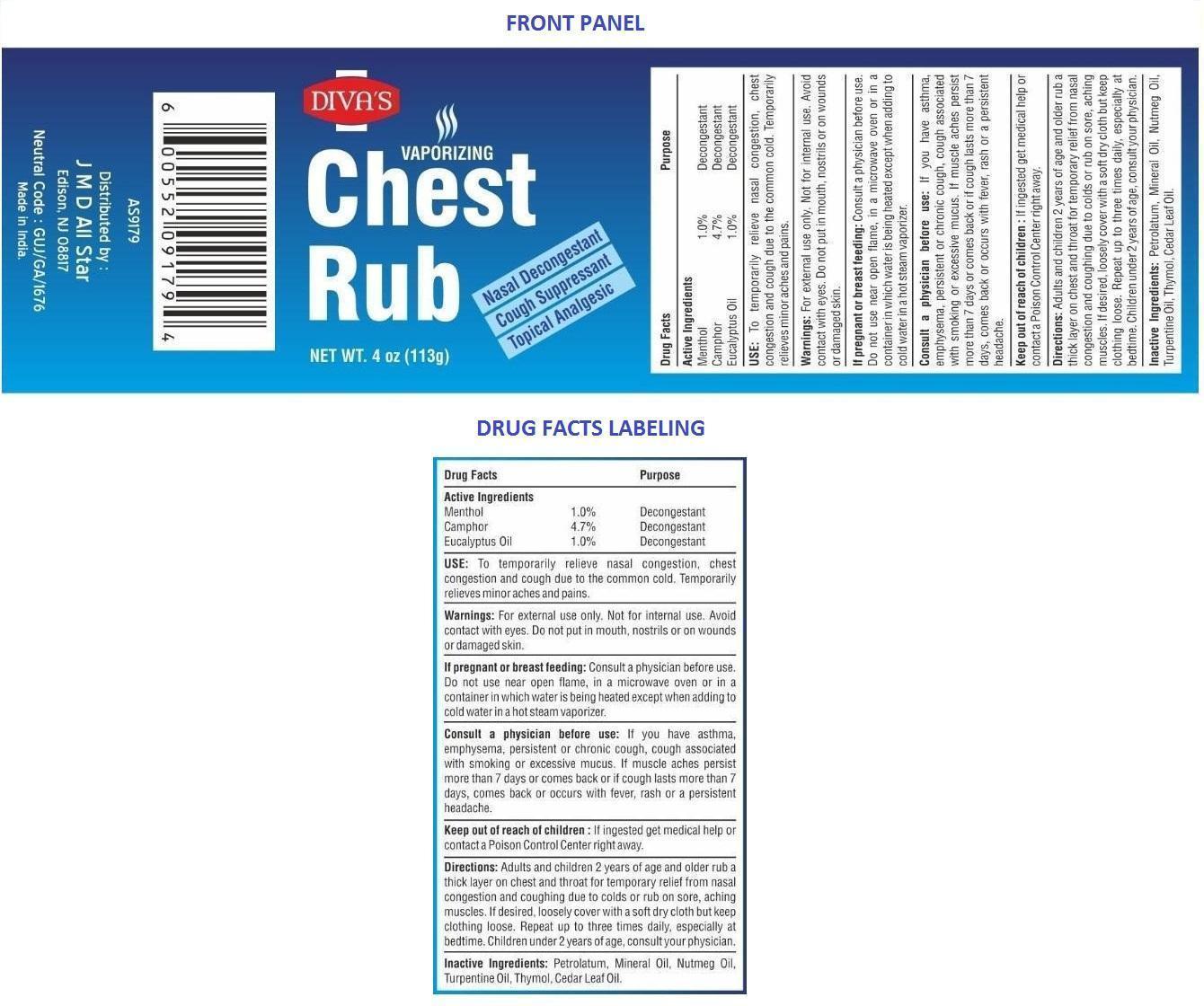 DRUG LABEL: Chest Rub
NDC: 69859-001 | Form: OINTMENT
Manufacturer: JT Cosmetics and Chemicals
Category: otc | Type: HUMAN OTC DRUG LABEL
Date: 20150601

ACTIVE INGREDIENTS: MENTHOL, UNSPECIFIED FORM 1 g/100 g; CAMPHOR (NATURAL) 4.7 g/100 g; EUCALYPTUS OIL 1 g/100 g
INACTIVE INGREDIENTS: PETROLATUM; MINERAL OIL; NUTMEG OIL; TURPENTINE OIL; THYMOL; CEDAR LEAF OIL

Chest Rub

Active Ingredients

Menthol

Camphor

Eucalyptus Oil

Purpose

Decongestant

Keep out of reach of children: If ingested get medical help or contact a Poison Control Center right away.

INDICATIONS AND USAGE

USE: To temporarily relieve nasal congestion, chest congestion and cough due to the common cold. Temporarily relieves minor aches and pains.

WARNINGS

Warnings: For external use only. Not for internal use. Avoid contact with eyes. Do not put in mouth, nostrils or on wounds or damaged skin.

If pregnant or breast feeding: Consult a physician before use. Do not use near open flame, in a microwave oven or in a container in which water is being heated except when adding to cold water in a hot steam vaporizer.

Consult a physician before use: If you have asthma, emphysema, persistent or chronic cough, cough associated with smoking or excessive mucus. If muscle aches persist more than 7 days or comes back or if cough lasts more than 7 days, comes back or occurs with fever, rash or a persistent headache.

DOSAGE AND ADMINISTRATION

Directions: Adults and children 2 years of age and older rub a thick layer on chest and throat for temporary relief from nasal congestion and coughing due to colds or rub on sore, aching muscles. If desired, loosely cover with a soft dry cloth but keep clothing loose. Repeat up to three times daily, especially at bedtime. Children under 2 years of age, consult your physician.

INACTIVE INGREDIENT

Inactive Ingredients: Petrolatum, Mineral Oil, Nutmeg Oil, Turpentine Oil, Thymol, Cedar Leaf Oil.

Distributed by

J M D All Star

Edison NJ 08817

Neutral Code : GUJ /GA/1676

Made in india.